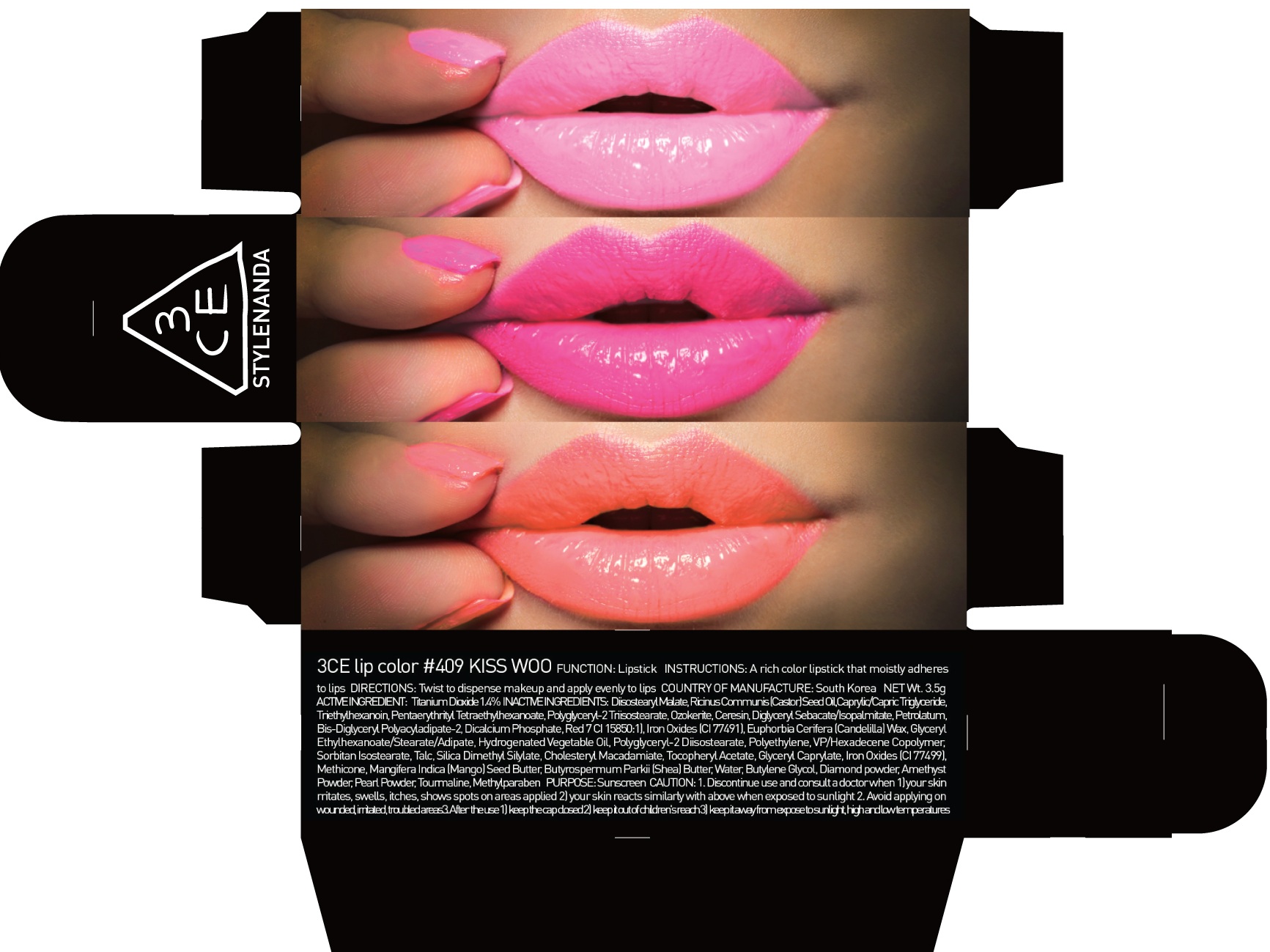 DRUG LABEL: 3CE LIP COLOR 409 KISS WOO
NDC: 60764-072 | Form: LIPSTICK
Manufacturer: Nanda Co., Ltd
Category: otc | Type: HUMAN OTC DRUG LABEL
Date: 20161007

ACTIVE INGREDIENTS: Titanium Dioxide 0.04 g/3.5 g
INACTIVE INGREDIENTS: Diisostearyl Malate; Triethylhexanoin

ACTIVE INGREDIENT

Active Ingredient: Titanium Dioxide 1.4%

INACTIVE INGREDIENT

Inactive Ingredients: Diisostearyl Malate, Ricinus Communis (Castor) Seed Oil, Caprylic/Capric Triglyceride, Triethylhexanoin, Pentaerythrityl Tetraethylhexanoate, Polyglyceryl-2 Triisostearate, Ozokerite, Ceresin, Diglyceryl Sebacate/Isopalmitate, Petrolatum, Bis-Diglyceryl Polyacyladipate-2, Dicalcium Phosphate, Red 7 (CI 15850:1), Iron Oxides (CI 77491), Euphorbia Cerifera (Candelilla) Wax, Glyceryl Ethylhexanoate/Stearate/Adipate, Hydrogenated Vegetable Oil, Polyglyceryl-2 Diisostearate, Polyethylene, VP/Hexadecene Copolymer, Sorbitan Isostearate, Talc, Silica Dimethyl Silylate, Cholesteryl Macadamiate, Tocopheryl Acetate, Glyceryl Caprylate, Iron Oxides (CI 77499), Methicone, Mangifera Indica (Mango) Seed Butter, Butyrospermum Parkii (Shea) Butter, Water, Butylene Glycol, Diamond powder, Amethyst Powder, Pearl Powder, Tourmaline, Methylparaben

PURPOSE

Purpose: Sunscreen

CAUTION

CAUTION: 1. Discontinue use and consult a doctor when - your skin irritates, swells, itches, shows spots on areas applied - your skin reacts similarly with above when exposed to sunlight 2. Avoid applying on wounded, irritated, troubled areas 3. After the use - keep the cap closed - keep it out of children's reach - keep it away from expose to sunlight, high and low temperatures

DESCRIPTION

INSTRUCTIONS: A rich color lipstick that moistly adheres to lips.

Directions: Twist to dispense makeup and apply evenly to lips